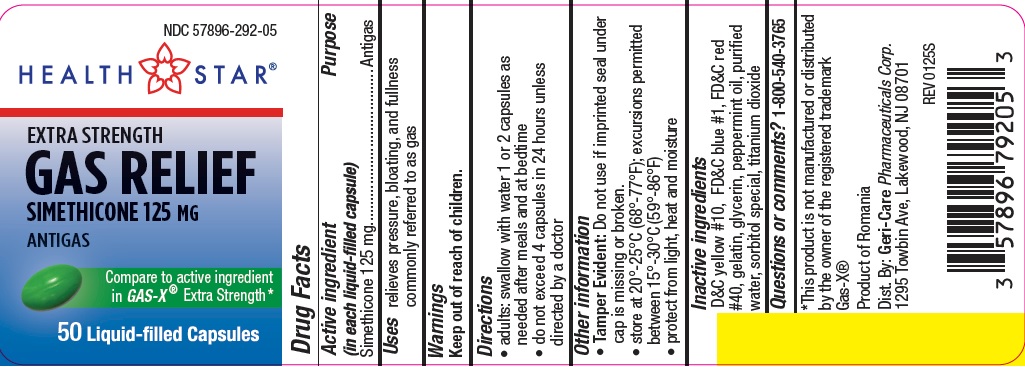 DRUG LABEL: EXTRA STRENGTH GAS RELIEF
NDC: 57896-292 | Form: CAPSULE, LIQUID FILLED
Manufacturer: Geri-Care Pharmaceuticals, Corp
Category: otc | Type: HUMAN OTC DRUG LABEL
Date: 20251210

ACTIVE INGREDIENTS: DIMETHICONE 125 mg/1 1
INACTIVE INGREDIENTS: WATER; D&C YELLOW NO. 10; GELATIN; FD&C RED NO. 40; FD&C BLUE NO. 1; GLYCERIN; PEPPERMINT OIL; SORBITOL SOLUTION; TITANIUM DIOXIDE

gc792S (292)

Active ingredient (in each liquid-filled capsule)

Simethicone 125 mg

Purpose

Antigas

Uses

relieves pressure, bloating, and fullness commonly referred to as gas

Warnings

Keep out of reach of children.

Directions

- adults: swallow with water 1 or 2 capsules as needed after meals and at bedtime
- do not exceed 4 capsules in 24 hours unless directed by a doctor

Other information

- Tamper Evident: Do not use if imprinted seal under cap is missing or broken.
- Product of Romania
- store at 20°-25°C (68°-77°F); excursions permitted between 15°-30°C (59°-86°F)
- protect from light, heat and moisture

Inactive ingredients

D&C yellow #10, FD&C blue #1, FD&C red #40, gelatin, glycerin, peppermint oil, purified water, sorbitol special, titanium dioxide

Questions or comments?

1-800-540-3765